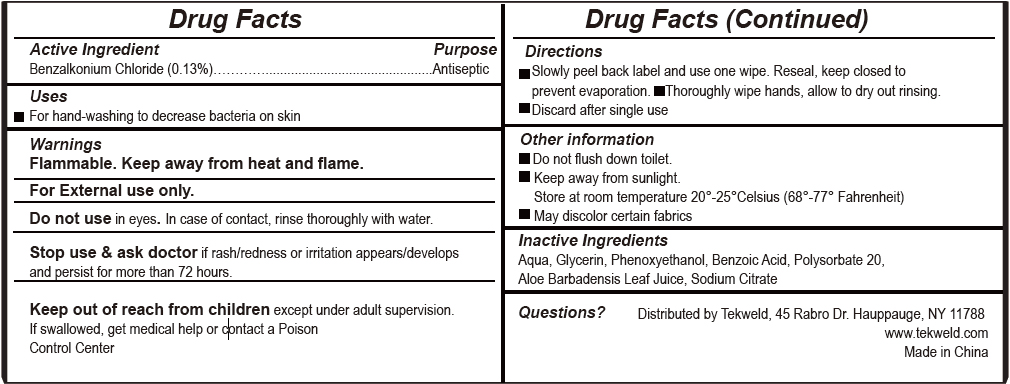 DRUG LABEL: Antibacterial Wet wipes
NDC: 73760-001 | Form: SWAB
Manufacturer: Zhejiang Easyclean Daily Chemical Co., Ltd.
Category: otc | Type: HUMAN OTC DRUG LABEL
Date: 20260211

ACTIVE INGREDIENTS: BENZALKONIUM CHLORIDE 0.13 g/100 g
INACTIVE INGREDIENTS: GLYCERIN; ALOE VERA LEAF; POLYSORBATE 20; PHENOXYETHANOL; BENZOIC ACID 2-(2,4,6-TRICHLOROPHENYL)HYDRAZIDE; WATER; SODIUM CITRATE

73760-001 ANTIBACTERIAL WET WIPES 0.13% benzalkonium chloride

Active Ingredient

Benzalkonium Chloride 0.13%

Purpose

Antiseptic

USE

For hand-washing to decrease bacteria on skin

Warning

Flammable. Keep away from heat and flame.
For External use only.
Do not use in eyes. In case of contact, rinse thoroughly with water.
Stop use & ask doctor if rash/redness or irritation appears/develops
and persist for more than 72 hours.

KEEP OUT OF REACH OF CHILDREN

Keep out of reach from children except under adult supervision.
If swallowed, get medical help or contact a Poison Control Center

Directions

Slowly peel back label and use one wipe. Reseal, keep closed to
prevent evaporation. Thoroughly wipe hands, allow to dry out rinsing.
Discard after single use
Other information
Do not flush down toilet.
Keep away from sunlight.
Store at room temperature 20°-25°Celsius (68°-77° Fahrenheit)
May discolor certain fabrics

Inactive ingredients

Aqua, Glycerin, Phenoxyethanol, Benzoic Acid, Polysorbate 20,
Aloe Barbadensis Leaf Juice, Sodium Citrate